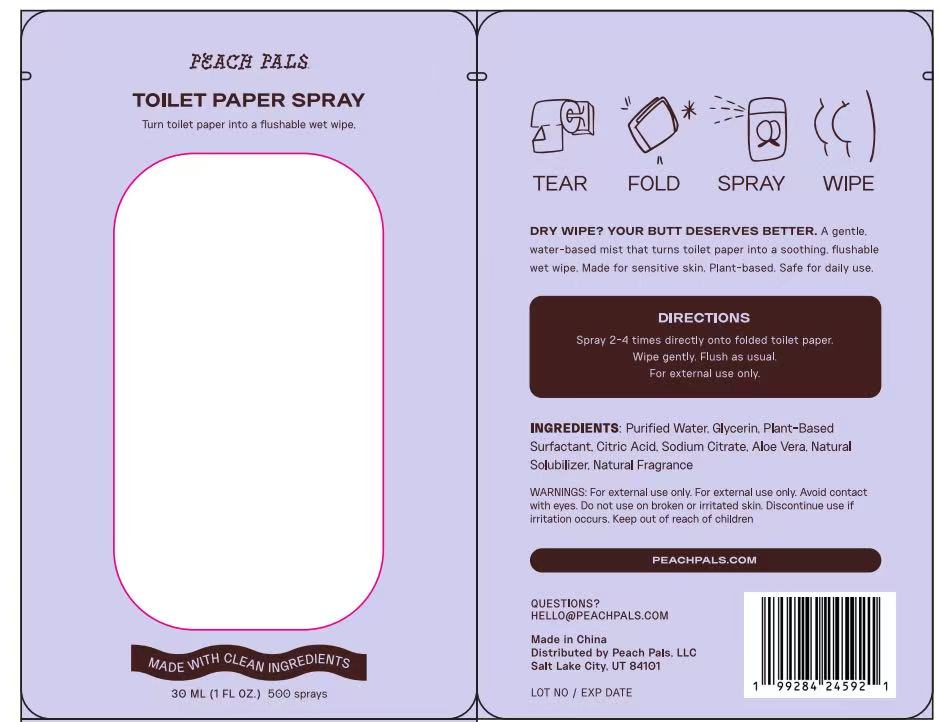 DRUG LABEL: TOILETPAPERSPRAY
NDC: 84778-097 | Form: LIQUID
Manufacturer: Guangzhou Yixin Cross-border E-commerce Co., Ltd.
Category: otc | Type: HUMAN OTC DRUG LABEL
Date: 20251009

ACTIVE INGREDIENTS: ALCOHOL 0.1 g/30 mL
INACTIVE INGREDIENTS: ALOE VERA LEAF; GLYCERIN; WATER

Active ingredients

Ethanol 65%

Purpose

Kills harmful microbes present on toilet seats and ensures a safe toilet experience. Can be used on toilet seats, flush handles, knobs, faucets, etc.

Uses:

For sanitizing toilet seats and hard suraces Can be used on hands when soap and water are not available.

Warnings

Far external use only
Flammable. Keep away from heat and flame
Do not use on broken or irritated skin
Avoid contact with eyes. If contact occurs, rinse thoroughly
Stop use if irritation or rash occurs
Keep out of reach of children

Dosage and administration

Application Method：

Shake the bottle well before use.
Hold the bottle 6-8 inches (15-20 cm) away from the toilet seat surface.
Spray evenly to cover the entire contact area of the toilet seat (including the seat ring and edges).
Allow the surface to air-dry completely (approximately 10-30 seconds, depending on ambient humidity) before use. No need to wipe with a cloth unless visible residue remains.

Recommended Dosage：
2-3 sprays per toilet seat (adjust based on seat size; ensure the surface is slightly damp but not dripping).

Do not use

1.FOR THE FOLLOWING SCENARIOS OR SURFACES

DO NOT ingest, inhale, or apply to mucous membranes (e.g., mouth, nose, eyes). This product is for external use only on hard surfaces or hands; internal use may cause irritation, allergic reactions, or toxicity.
AVOID use on non - hard surfaces (e.g., fabrics, leather, silk), as it may cause staining, material damage, or reduced sanitization efficacy. Use only on toilet seats, ceramic, metal, plastic, or other smooth hard surfaces.
DO NOT apply to open wounds, cuts, or severely irritated skin (e.g., eczema, blisters). Ingredients may exacerbate pain or increase infection risk.

2. FOR SPECIFIC POPULATIONS

DO NOT use if allergic to any ingredient (e.g., alcohol, aloe vera, essential oils, benzalkonium chloride). Discontinue use immediately if rash, itching, or irritation occurs.
CHILDREN UNDER 6 YEARS OLD SHOULD NOT use unsupervised due to risks of eye contact, ingestion, or excessive application on sensitive skin.

3. AVOID MIXING WITH OTHER PRODUCTS

NEVER mix with soaps, detergents, or other disinfectants (e.g., chlorine - based cleaners). Mixtures may neutralize active ingredients, reduce efficacy, or generate harmful fumes (especially if product contains alcohol).

4. IN HAZARDOUS ENVIRONMENTS

DO NOT use or store near open flames, heat sources, or flammable materials (e.g., stoves, lighters, gasoline). Product contains flammable ingredients (e.g., alcohol, essential oils); keep away from temperatures above 30°C (86°F) and direct sunlight.

5. IF PRODUCT QUALITY CHANGES

DO NOT use if the product is cloudy, separated, has an unusual odor, or the nozzle is clogged (may indicate spoilage or contamination, compromising safety and effectiveness).

WHEN USING THIS PRODUCT

1. FOR TOILET SEAT & HARD SURFACE SANITIZATION

SHAKE WELL before use to ensure uniform distribution of active ingredients.
MAINTAIN A DISTANCE of 6-8 inches (15-20 cm) when spraying on toilet seats; 8-10 inches (20-25 cm) for other hard surfaces (e.g., door handles, sinks).
ALLOW SURFACES TO AIR - DRY COMPLETELY (10-30 seconds) before contact; no wiping needed unless visible residue remains.
LIMIT USE TO HARD, NON - POROUS SURFACES (e.g., ceramic, metal, plastic) to avoid damage to fabrics or leather.

2. FOR EMERGENCY HAND SANITIZATION

APPLY 1-2 SPRAYS directly to palms (no need for water), then rub hands thoroughly for 20 seconds, covering all surfaces (between fingers, back of hands, nails).
AVOID USE ON DAMAGED SKIN (cuts, rashes) and rinse immediately if contact with eyes occurs.
CHILDREN UNDER 6 SHOULD BE SUPERVISED to prevent eye contact or ingestion.

3. GENERAL PRECAUTIONS

AVOID INHALATION OF SPRAY MIST; use in well - ventilated areas (open windows or doors when applying in enclosed spaces like bathrooms).
PROTECT EYES AND SKIN by wearing gloves if prolonged contact is needed (e.g., cleaning multiple surfaces).
DO NOT OVERSPRAY; excessive use may cause residue buildup or damage to painted/coated surfaces.

4. STORAGE & DISPOSAL

STORE AT ROOM TEMPERATURE (15-30°C/59-86°F) away from direct sunlight, heat, or freezers (cold temperatures may cause clouding, but product is usable after warming to room temperature).
KEEP BOTTLE TIGHTLY CLOSED when not in use to prevent evaporation of active ingredients (e.g., alcohol).
DISPOSE OF EMPTY BOTTLES ACCORDING TO LOCAL REGULATIONS; do not incinerate or expose to high heat.

STOP USE AND CONSULT A PROFESSIONAL IF:

1. Adverse Reactions Occur After Use

Discontinue use immediately if skin develops redness, itching, burning, rash, or other allergic reactions (e.g., localized redness or hives at the contact site). Rinse the affected area with clean water to remove residual spray. If symptoms persist (e.g., prolonged itching or swelling), consult a doctor or pharmacist promptly to prevent further irritation.
If the product is accidentally ingested or inhaled, leading to nausea, vomiting, difficulty breathing, or dizziness, seek medical help immediately. Bring the product packaging (with ingredient list) to assist healthcare providers in rapid assessment and treatment.

2. Product Condition Is Abnormal

Stop use at once if the spray becomes cloudy, separated, has an unusual odor, or the nozzle is clogged and cannot spray properly. These signs may indicate ingredient deterioration or contamination, which could reduce sanitization efficacy or pose safety risks. Do not attempt to unclog the nozzle with sharp objects or continue using the product.
Discontinue use if the product exceeds its expiration date or the recommended "use - by period after opening" (e.g., "use within 6 months of opening"). Even if the product appears normal, active ingredients may have degraded and lost effectiveness.

3. Misuse Causes Safety Risks

Cease use immediately if the product is accidentally applied to mucous membranes (e.g., eyes, mouth, nose) or open wounds. If irritation occurs (e.g., eye stinging or tearing), flush the affected area with large amounts of running water for at least 15 minutes. If symptoms persist (e.g., blurred vision or persistent pain), seek medical attention without delay.
Stop use and move to a safe area if the product is exposed to open flames or high - temperature environments (e.g., spraying near a gas stove) during use, resulting in spray vaporization or abnormal reactions. Check the product for damage before considering future use.

4. Abnormal Reactions in Special Populations

Discontinue use if special populations (children under 6, pregnant women, lactating mothers, or the elderly) experience unusual sensitivity reactions after use—such as redness on a child’s hands or discomfort in pregnant women. Consult a doctor immediately to determine if the reaction is caused by individual differences.

KEEP OUT OF REACH OF CHILDREN

1. STORAGE PRECAUTIONS TO PREVENT ACCESS
Store the product at a height out of children’s reach (recommended ≥5 feet/1.5 meters above the ground), such as on upper kitchen shelves, locked cabinets, or in closets.
Avoid storing in visible or accessible areas (e.g., low drawers, bathroom counters, or near children’s play zones), as kids may be attracted to the bottle’s shape or scent.
Use child - resistant packaging features if available (e.g., push - and - twist caps, safety locks), and ensure they are properly engaged after each use.
2. RISKS OF CHILDREN’S ACCIDENTAL EXPOSURE
Ingestion hazard: Children may mistake the spray for a beverage or candy - scented product. If ingested, even small amounts of alcohol, essential oils, or disinfectant ingredients can cause nausea, vomiting, or central nervous system depression.
Eye/skin irritation: Accidental spraying in the eyes or on the skin (especially sensitive areas like the face) may lead to redness, burning, or allergic reactions, particularly if the product contains alcohol or concentrated essential oils.
Inhalation risk: Children inhaling spray mist in enclosed spaces may experience respiratory irritation, coughing, or difficulty breathing.
3. SUPERVISION GUIDELINES FOR USE
Never leave children unattended during use: Ensure kids are kept at a safe distance (≥3 feet/1 meter) while spraying, and wait until the surface is fully dry before allowing them to interact with treated areas (e.g., toilet seats).
Teach children about product safety: Explain that the spray is "not a toy" and demonstrate proper storage locations, especially for older kids who may understand simple warnings.
Wash hands after use around children: Adults should rinse their hands thoroughly after applying the spray to prevent transferring residues to children during hugs, feeding, or play.
4. EMERGENCY ACTIONS FOR ACCIDENTAL EXPOSURE
If ingested: Do not induce vomiting. Call a poison control center (e.g., 1 - 800 - 222 - 1222 in the U.S.) or seek emergency medical help immediately, providing the product’s ingredient list and volume consumed.
If in eyes: Flush the child’s eyes with lukewarm water for 15 minutes, holding the eyelids open; consult a pediatrician or ophthalmologist if redness or discomfort persists.
If on skin: Wash the affected area with mild soap and water; apply a gentle moisturizer if irritation occurs, and seek medical advice for severe reactions (e.g., blistering).

Inactive ingredients

Purified Water. Glycerin, Plant-BasedSurfactant, Citric Acid, Sodium Citrate, Aloe Vera, NaturalSolubilizer, Natural Fragrance